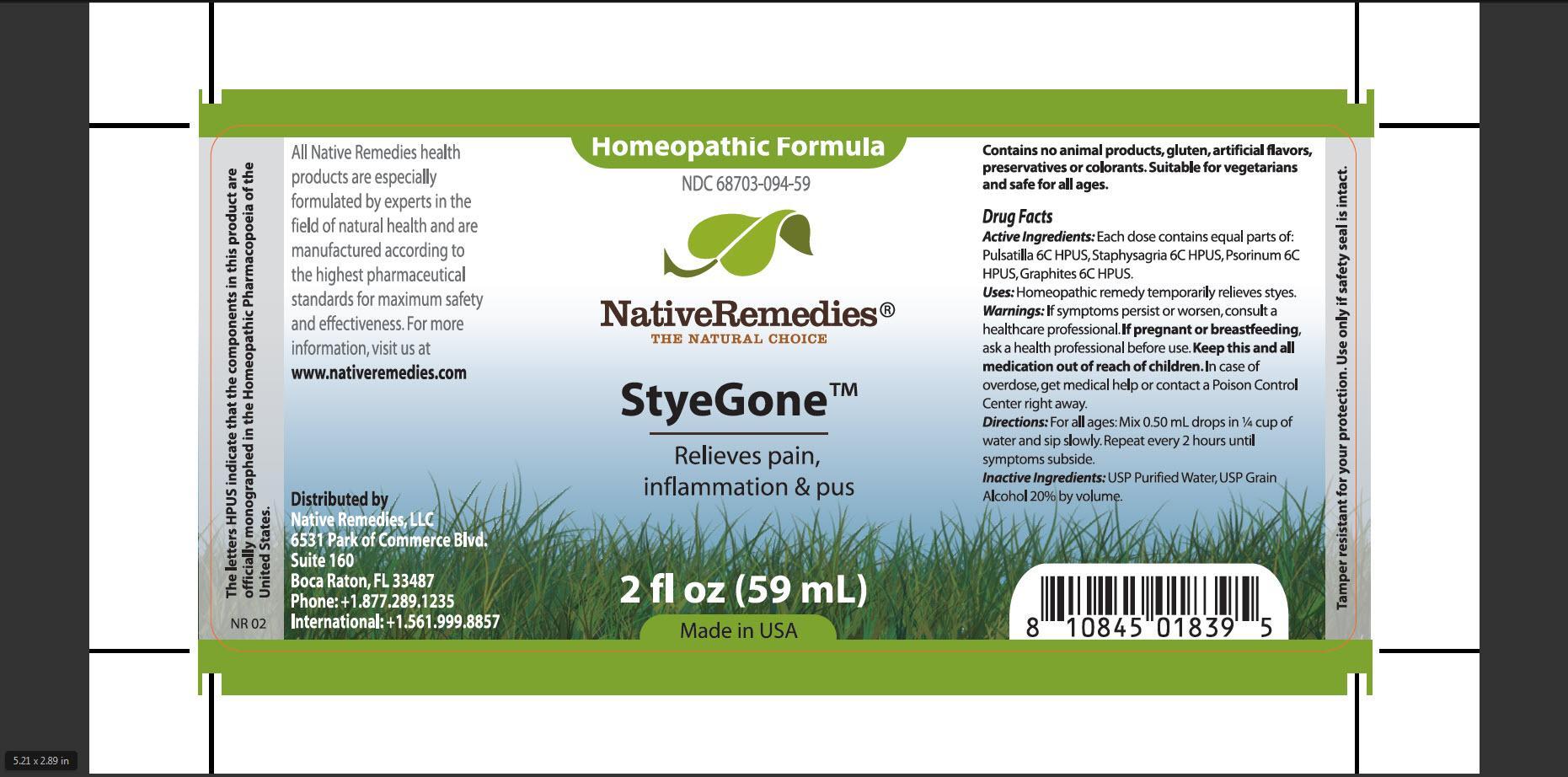 DRUG LABEL: StyeGone
NDC: 68703-094 | Form: TINCTURE
Manufacturer: Native Remedies, LLC
Category: homeopathic | Type: HUMAN OTC DRUG LABEL
Date: 20130327

ACTIVE INGREDIENTS: PULSATILLA VULGARIS 6 [hp_C]/1 mL; DELPHINIUM STAPHISAGRIA SEED 6 [hp_C]/1 mL; SCABIES LESION LYSATE (HUMAN) 6 [hp_C]/1 mL; GRAPHITE 6 [hp_C]/1 mL
INACTIVE INGREDIENTS: WATER; ALCOHOL

StyeGone

PURPOSE

Relieves pain, inflammation and pus

ACTIVE INGREDIENT

Active Ingredients:Each dose contains equal parts of: Pulsatilla 6C HPUS, Staphysagria 6C HPUS, Psorinum 6C HPUS, Graphites 6C HPUS

INDICATIONS AND USAGE

Uses: Homeopathic remedy temporarily relieves styes

WARNINGS

Warnings: If symptoms persist or worsen, consult a healthcare professional

PREGNANCY OR BREAST FEEDING

If pregnant of breastfeeding, ask a health professional before use

KEEP OUT OF REACH OF CHILDREN

Keep this and all medication out of reach of children

OVERDOSAGE

In case of overdose, get medical help or contact a Poison Control Center right away

DOSAGE AND ADMINISTRATION

Directions: For all ages: Mix 0.50 mL drops in 1/4 cup of water and sip slowly. Repeat every 2 hours until symptoms subside

INACTIVE INGREDIENT

Inactive Ingredients: USP Purified Water, USP Grain Alcohol 20% by volume

PATIENT COUNSELING INFORMATION

The letters HPUS indicate that the components in this product are officially monographed in the Homeopathic Pharmacopoeia of the United States

All Native Remedies health products are especially formulated by experts in the field of natural health and are manufactured according to the highest pharmaceutical standards for maximum safety and effectiveness. For more information, visit us at www.nativeremedies.com

Distributed by
Native Remedies, LLC
6531 Park of Commerce Blvd.
Suite 160
Boca Raton, Fl 33487
Phone: +1.877.289.1235
International: +1.561.999.8857

Contains no animal products, gluten, artificial flavors, preservatives or colorants. Suitable for vegetarians and safe for all ages

STORAGE AND HANDLING

Tamper resistant for your protection. Use only if safety seal is intact